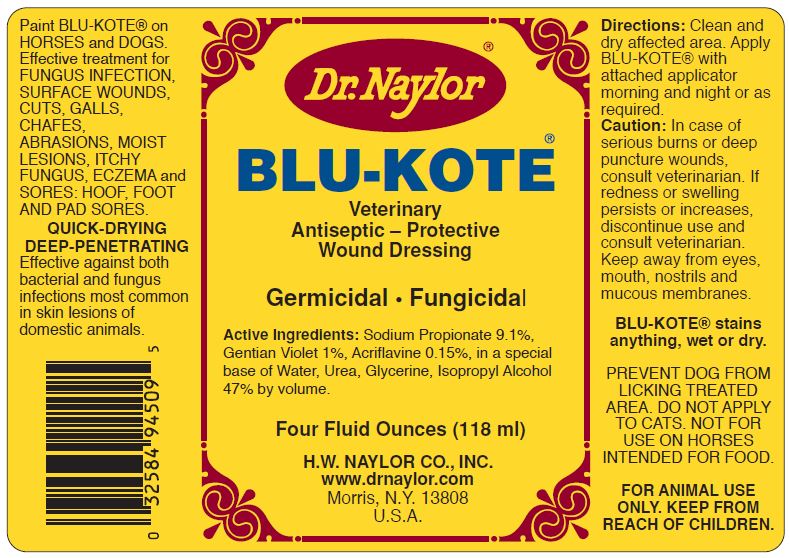 DRUG LABEL: BLU-KOTE Veterinary Antiseptic-Protective Wound Dressing 
NDC: 15878-211 | Form: LIQUID
Manufacturer: H. W. Naylor Company Inc.
Category: animal | Type: OTC ANIMAL DRUG LABEL
Date: 20130104

ACTIVE INGREDIENTS: Sodium Propionate 90 mg/1000 mL; Gentian Violet 10 mg/1000 mL; Acriflavine 1.7 mg/1000 mL
INACTIVE INGREDIENTS: Water; Urea; Isopropyl Alcohol

BLU-KOTE® Veterinary Antiseptic-Protective Wound Dressing

Active Ingredients

Sodium Propionate 9.1%, Gentian Violet 1%, Acriflavine 0.15%

Purpose

Effective treatment for FUNGUS INFECTION, SURFACE WOUNDS, CUTS, GALLS, CHAFES, ABRASIONS, MOIST LESIONS, ITCHY FUNGUS, ECZEMA and SORES: HOOF, FOOT AND PAD SORES for HORSES and DOGS.

Directions

PAINT ON HORSES and DOGS.

Clean and dry affected area.

Apply BLU-KOTE with attached applicator morning and night or as required.

Safety

CAUTION: In case of serious burns, deep or puncture wounds, consult veterinarian.

If redness, irritation or swelling persists or increases, discontinue use and consult veterinarian.

Keep away from eyes, mouth, nostrils and mucous membranes.

Do not apply to large areas of broken skin.

BLUE-KOTE stains anything, wet or dry.

PREVENT DOG FROM LICKING TREATED AREA.

DO NOT APPLY TO CATS.

NOT FOR USE ON HORSES INTENDED FOR FOOD.

FOR ANIMAL USE ONLY.

Other Ingredients

Water, Urea, Glycerine, Isopropyl Alcohol 47% by volume.

Principal Display Panel

Dr. Naylor®
BLU-KOTE®
Veterinary Antiseptic - Protective Wound Dressing
Germicidal Fungicidal
Four Fluid Ozs. (118 ml)
H.W. NAYLOR CO., INC.
www.drnaylor.com
Morris, N.Y. 13808
U.S.A.
QUICK-DRYING DEEP-PENETRATING
Effective against both bacterial and fungus infections most common in skin lesions of domestic animals.